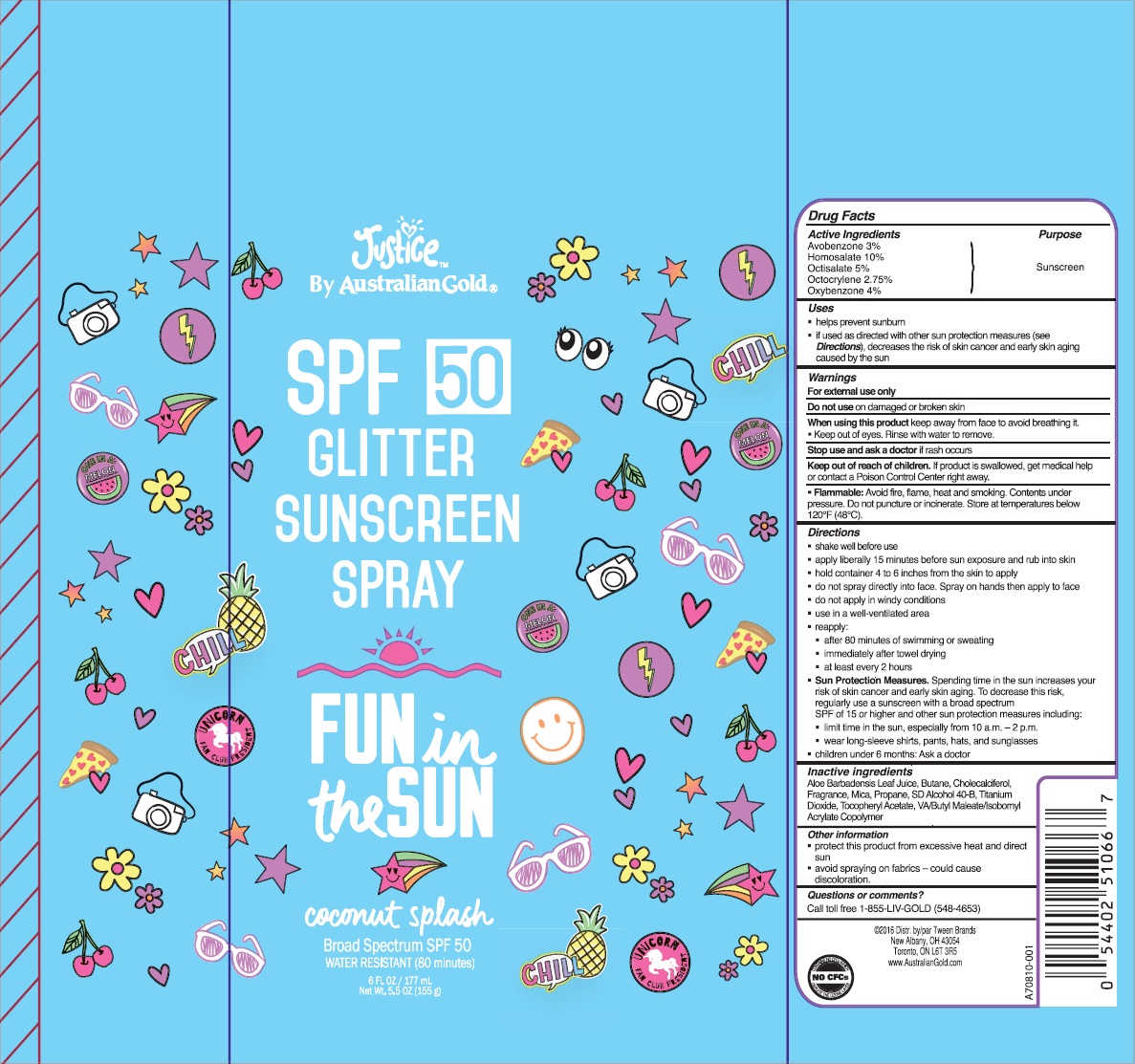 DRUG LABEL: Australian Gold
NDC: 13630-0121 | Form: SPRAY
Manufacturer: Prime Packaging Inc.
Category: otc | Type: HUMAN OTC DRUG LABEL
Date: 20200117

ACTIVE INGREDIENTS: AVOBENZONE 26.07 mg/1 mL; HOMOSALATE 86.9 mg/1 mL; OCTISALATE 43.45 mg/1 mL; OCTOCRYLENE 23.9 mg/1 mL; OXYBENZONE 34.76 mg/1 mL
INACTIVE INGREDIENTS: TITANIUM DIOXIDE; BUTANE; ALOE VERA LEAF; PROPANE; CHOLECALCIFEROL; MICA; .ALPHA.-TOCOPHEROL ACETATE; ALCOHOL; DIBUTYL MALEATE

Justice SPF 50 Glitter Sunscreen

Active Ingredients

Avobenzone 3%

Homosalate 10%

Octisalate 5%

Octocrylene 2.75%

Oxybenzone 4%

Purpose

Sunscreen

Uses

- helps prevent sunburn
- if used as directed with other sun protection measures (see Directions), decreases the risk of skin cancer and early skin aging caused by the sun

Warnings

For external use only

Do not use on damaged or broken skin

When using this product keep away from face to avoid breathing it.

- Keep out of eyes. Rinse with water to remove.

Stop use and ask a doctor if rash occurs

Keep out of reach of children. If product is swallowed, get medical help or contact a Poison Control Center right away.

Flammable: Avoid fire, flame, heat and smoking. Contents under pressure. Do not puncture or incinerate. Store at temperatures below 120°C (48°C).

Directions

- shake well before use
- apply liberally 15 minutes before sun exposure and rub into skin
- hold container 4 to 6 inches from the skin to apply
- do not spray directly into face. Spray on hands then apply to face
- do not apply in windy conditions
- use in a well-ventilated area
- reapply:
- after 80 minutes of swimming and sweating
- immediately after towel drying
- at least every 2 hours
- Sun Protection Measures. Spending time in the sun increases your risk of skin cancer and early skin aging. To decrease this risk, regularly use a sunscreen with a broad spectrum SPF of 15 or higher and other sun protection measures including:
- limit time in the sun, especially from 10 a. m. - 2 p. m.
- wear long-sleeve shirts, pants, hats, and sunglasses
- children under 6 months: Ask a doctor

INACTIVE INGREDIENT

Aloe Barbadensis Leaf Juice, Butane, Cholecalciferol, Fragrance, Mica, Propane, SD Alcohol 40-B, Titanium Dioxide, Tocopheryl Acetate, VA/Butyl Maleate/Isobornyl Acrylate Copolymer

Other Information

- protect this product from excessive heat and direct sun
- avoid spraying on fabrics - could cause discoloration.

Question or comments?

Call toll free 1-855-LIV-GOLD (548-4653)